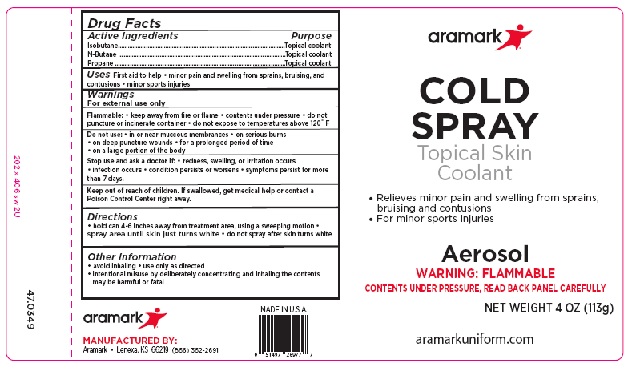 DRUG LABEL: AramarkCold Spray
NDC: 81238-2982
Manufacturer: Western First Aid Safety dba Aramark
Category: other | Type: OTC MEDICAL DEVICE LABEL
Date: 20130409

Aramark Cold Spray

Active Ingredients
Isobutane
N-Butane
Propane

Purpose
Isobutane.............................Topical coolant
N-Butane ............................Topical coolant
Propane ..............................Topical coolant

INDICATIONS AND USAGE

Uses First aid to help • minor pain and swelling from sprains, bruising, and
contusions • minor sports injuries

Warnings
For external use only
Flammable: • keep away from fire or flame • contents under pressure • do not
puncture or incinerate container • do not expose to temperatures above 120ο F
Do not use: • in or near muccous membrances • on serious burns
• on deep puncture wounds • for a prolonged period of time
• on a large portion of the body
Stop use and ask a doctor if: • redness, swelling, or irritation occurs
• infection occurs • condition persists or worsens • symptoms persist for more
than 7 days.
Keep out of reach of children. If swallowed, get medical help or contact a
Poison Control Center right away.

Directions
• hold can 4-6 inches away from treatment area, using a sweeping motion •
spray area until skin just turns white • do not spray after skin turns white

Other Information
• avoid inhaling • use only as directed
• intentional misuse by deliberately concentrating and inhaling the contents
may be harmful or fatal

Principal Display

aramark

COLD
SPRAY
Topical Skin
Coolant

• Relieves minor pain and swelling from sprains,
bruising and contusions
• For minor sports injuries

Aerosol
WARNING: FLAMMABLE
CONTENTS UNDER PRESSURE, READ BACK PANEL CAREFULLY

NET WEIGHT 4 OZ (113g)

aramarkuniform.com

MANUFACTURED BY:

Aramark • Lenexa, KS 66219 (866) 362-2691

res